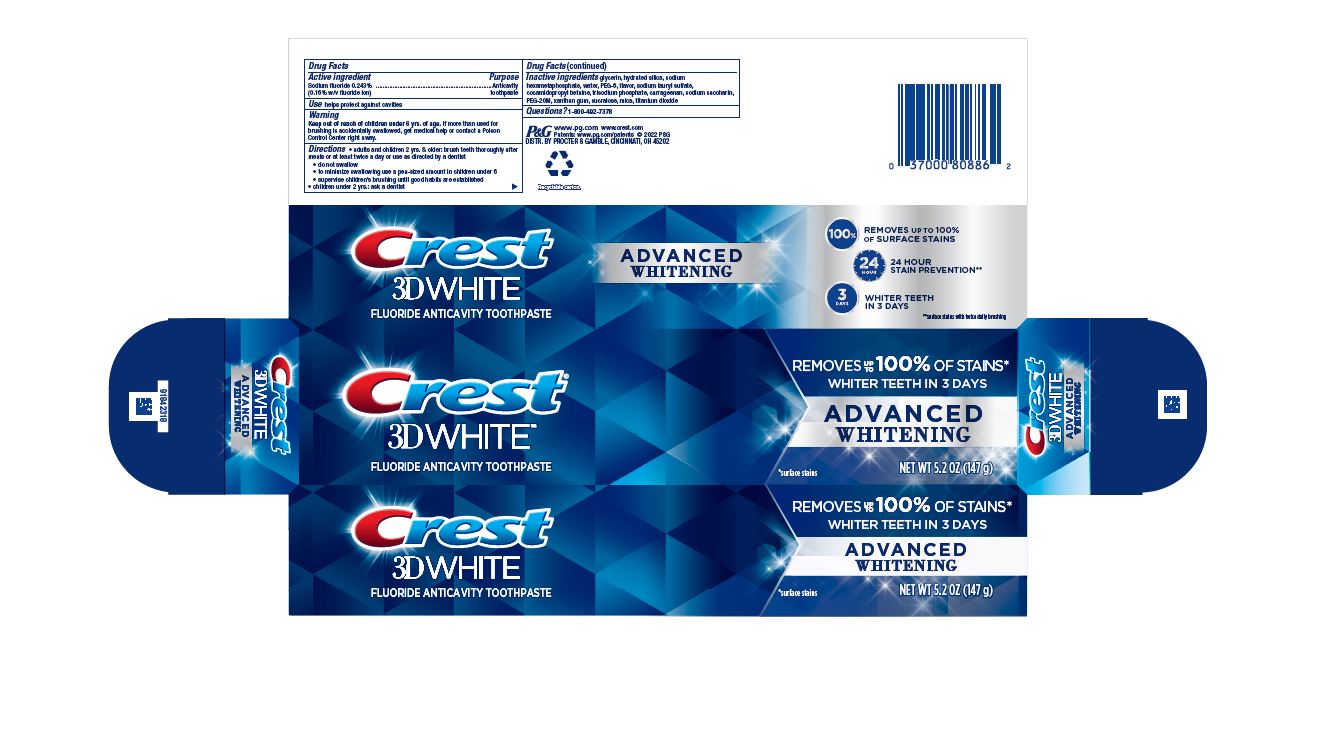 DRUG LABEL: Crest 3D White
NDC: 69423-853 | Form: PASTE, DENTIFRICE
Manufacturer: The Procter & Gamble Manufacturing Company
Category: otc | Type: HUMAN OTC DRUG LABEL
Date: 20250731

ACTIVE INGREDIENTS: SODIUM FLUORIDE 1.6 mg/1 g
INACTIVE INGREDIENTS: XANTHAN GUM; WATER; GLYCERIN; HYDRATED SILICA; SODIUM POLYMETAPHOSPHATE; SODIUM LAURYL SULFATE; POLYETHYLENE GLYCOL 300; POLYETHYLENE OXIDE 900000; SACCHARIN SODIUM; COCAMIDOPROPYL BETAINE; MICA; TITANIUM DIOXIDE; SODIUM PHOSPHATE, TRIBASIC, ANHYDROUS; CARRAGEENAN; SUCRALOSE

Crest 3D White Advanced Whitening

Drug Facts

Active ingredient

Sodium fluoride 0.243% (0.16% w/v fluoride ion)

Purpose

Anticavity toothpaste

Use

helps protect against cavities

Warning

Keep out of reach of children under 6 yrs. of age. If more than used for brushing is accidentally swallowed, get medical help or contact a Poison Control Center right away.

Directions

- adults and children 2 yrs. & older: brush teeth thoroughly after meals or at least twice a day or use as directed by a dentist
- do not swallow
- to minimize swallowing use a pea-sized amount in children under 6
  - supervise children's brushing until good habits are established
- children under 2 yrs.: ask a dentist

Inactive ingredients

glycerin, hydrated silica, sodium hexametaphosphate, water, PEG-6, flavor, sodium lauryl sulfate, cocamidopropyl betaine, trisodium phosphate, carrageenan, sodium saccharin, PEG-20M, xanthan gum, sucralose, mica, titanium dioxide

Questions?

1-800-492-7378

DISTR. BY PROCTER & GAMBLE, CINCINNATI, OH 45202

PRINCIPAL DISPLAY PANEL - 147 g Tube Carton

Crest®

3D WHITE™
FLUORIDE ANTICAVITY TOOTHPASTE

REMOVES UP TO 100% OF STAINS*

WHITER TEETH IN 3 DAYS

ADVANCED WHITENING

*surface stains

NET WT 5.2 OZ (147 g)